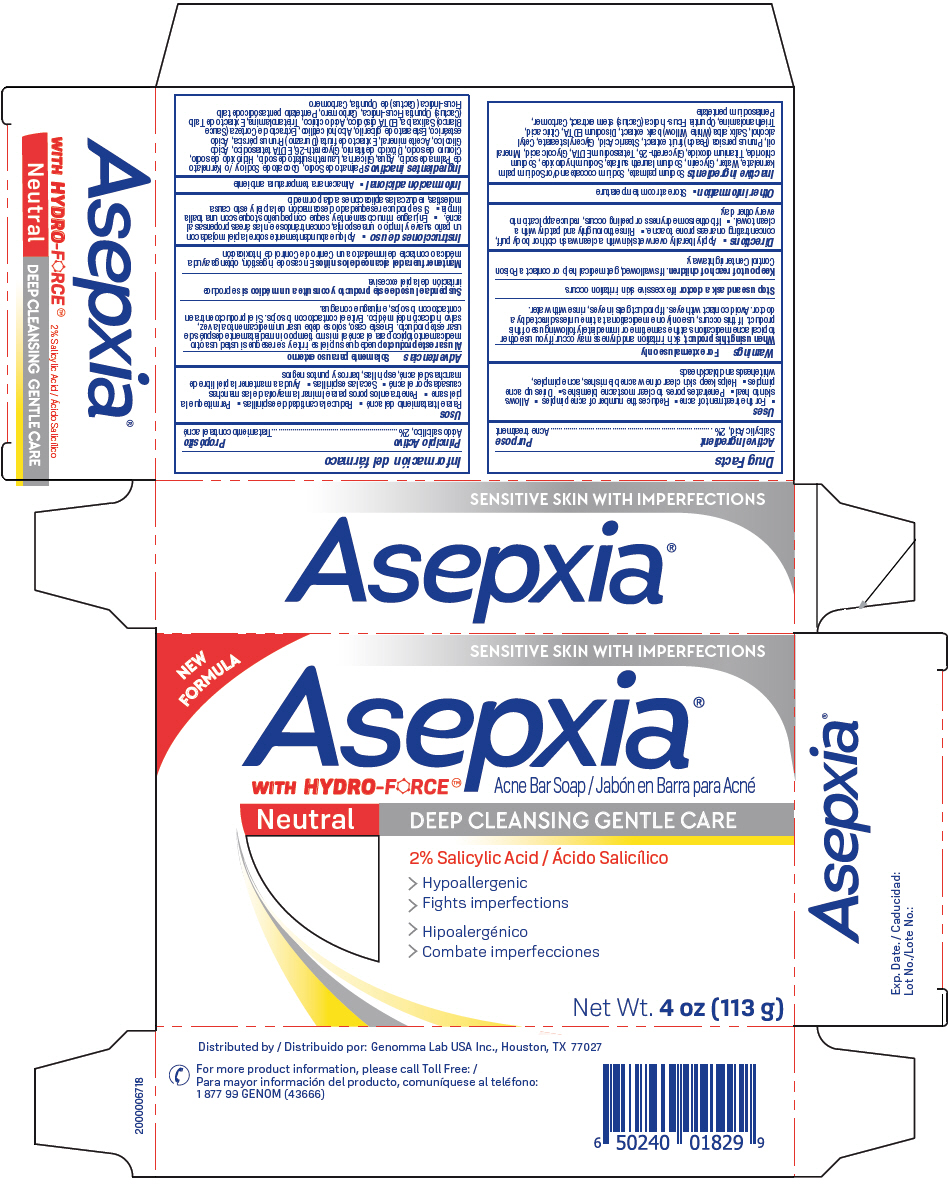 DRUG LABEL: Asepxia Neutral Acne Bar
NDC: 50066-802 | Form: SOAP
Manufacturer: Genomma Lab USA
Category: otc | Type: HUMAN OTC DRUG LABEL
Date: 20231106

ACTIVE INGREDIENTS: SALICYLIC ACID 2 g/100 g
INACTIVE INGREDIENTS: SODIUM PALMATE; SODIUM COCOATE; SODIUM PALM KERNELATE; WATER; GLYCERIN; SODIUM LAURETH-3 SULFATE; SODIUM HYDROXIDE; SODIUM CHLORIDE; TITANIUM DIOXIDE; GLYCERETH-26; EDETATE SODIUM; GLYCOLIC ACID; MINERAL OIL; PEACH; STEARIC ACID; GLYCERYL MONOSTEARATE; CETYL ALCOHOL; EDETATE DISODIUM ANHYDROUS; CITRIC ACID MONOHYDRATE; TROLAMINE; OPUNTIA FICUS-INDICA STEM; CARBOMER HOMOPOLYMER, UNSPECIFIED TYPE; PENTASODIUM PENTETATE

Asepxia Neutral Acne Bar Soap®

Active Ingredient

Salicylic Acid, 2%

Purpose

Acne treatment

Uses

- For the treatment of acne
- Reduces the number of acne pimples
- Allows skin to heal
- Penetrates pores to clear most acne blemishes
- Dries up acne pimples
- Helps keep skin clear of new acne blemishes, acne pimples, whiteheads and blackheads

Warnings

For external use only

WHEN USING

, skin irritation and dryness may occur if you use other topical acne medications at the same time or immediately following use of this product. If this occurs, use only one medication at a time unless directed by a doctor. Avoid contact with eyes. If product gets in eyes, rinse with water. When using this product

STOP USE

excessive skin irritation occurs Stop use and ask a doctor if

KEEP OUT OF REACH OF CHILDREN

. If swallowed, get medical help or contact a Poison Control Center right away. Keep out of reach of children

Directions

- Apply liberally over wet skin with a clean wash cloth or body puff, concentrating on areas prone to acne.
- Rinse thoroughly and pat dry with a clean towel.
- If bothersome dryness or peeling occurs, reduce application to every other day.

Other information

- Store at room temperature

Inactive ingredients

Sodium palmate, Sodium cocoate and/or Sodium palm kernelate, Water, Glycerin, Sodium laureth sulfate, Sodium hydroxide, Sodium chloride, Titanium dioxide, Glycereth-26, Tetrasodium EDTA, Glycolic acid, Mineral oil, Prunus persica (Peach) fruit extract, Stearic Acid, Glyceryl stearate, Cetyl alcohol, Salix alba (White Willow) bark extract, Disodium EDTA, Citric acid, Triethanolamine, Opuntia Ficus-Indica (Cactus) stem extract, Carbomer, Pentasodium pentetate

QUESTIONS

For more product information, please call Toll Free: 1 877 99 GENOM (43666)

Distributed by: Genomma Lab USA Inc., Houston, TX 77027

PRINCIPAL DISPLAY PANEL - 113 g Bar Carton

NEW FORMULA

SENSITIVE SKIN WITH IMPERFECTIONS

™ Acne Bar Soap Asepxia® WITH HYDRO-FORCE

DEEP CLEANSING GENTLE CARE Neutral

2% Salicylic Acid

> Hypoallergenic

> Fights imperfections

Net Wt. 4 oz (113 g)